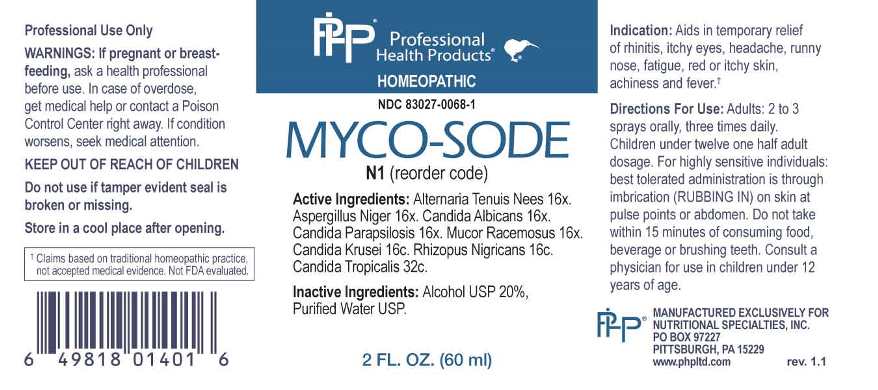 DRUG LABEL: Myco Sode
NDC: 83027-0068 | Form: SPRAY
Manufacturer: Nutritional Specialties, Inc.
Category: homeopathic | Type: HUMAN OTC DRUG LABEL
Date: 20240911

ACTIVE INGREDIENTS: ALTERNARIA ALTERNATA 16 [hp_X]/1 mL; ASPERGILLUS NIGER VAR. NIGER 16 [hp_X]/1 mL; CANDIDA ALBICANS 16 [hp_X]/1 mL; CANDIDA PARAPSILOSIS 16 [hp_X]/1 mL; MUCOR RACEMOSUS 16 [hp_X]/1 mL; ISSATCHENKIA ORIENTALIS WHOLE 16 [hp_C]/1 mL; RHIZOPUS STOLONIFER 16 [hp_C]/1 mL; CANDIDA TROPICALIS 32 [hp_C]/1 mL
INACTIVE INGREDIENTS: WATER; ALCOHOL

DRUG FACTS:

ACTIVE INGREDIENTS:

Alternaria Tenuis Nees 16X, Aspergillus Niger 16X, Candida Albicans 16X, Candida Parapsilosis 16X, Mucor Racemosus 16X, Candida Krusei 16C, Rhizopus Nigricans 16C, Candida Tropicalis 32C.

PURPOSE:

Aids in temporary relief of rhinitis, itchy eyes, headache, runny nose, fatigue, red or itchy skin†

†Claims based on traditional homeopathic practice, not accepted medical evidence. Not FDA evaluated.

WARNINGS:

Professional Use Only

If pregnant or breast-feeding, ask a health professional before use.

In case of overdose, get medical help or contact a Poison Control Center right away.

If condition worsens, seek medical attention.

KEEP OUT OF REACH OF CHILDREN

Do not use if tamper evident seal is broken or missing.

Store in a cool place after opening

KEEP OUT OF REACH OF CHILDREN:

In case of overdose, get medical help or contact a Poison Control Center right away.

DIRECTIONS:

Adults: 2 to 3 sprays orally, three times daily. Children under twelve one half adult dosage.

For highly sensitive individuals: best tolerated administration is through imbrication (RUBBING IN) on skin at pulse points or abdomen.

Do not take within 15 minutes of consuming food, beverage or brushing teeth. Consult a physician for use in children under 12 years of age.

INDICATIONS:

Aids in temporary relief of rhinitis, itchy eyes, headache, runny nose, fatigue, red or itchy skin†

†Claims based on traditional homeopathic practice, not accepted medical evidence. Not FDA evaluated.

INACTIVE INGREDIENTS:

Alcohol USP 20%, Purified Water USP.

QUESTIONS:

MANUFACTURED EXCLUSIVELY FOR

NUTRITIONAL SPECIALTIES, INC.

PO BOX 97227

PITTSBURG, PA 15229

www.phpltd.com

PACKAGE LABEL DISPLAY:

Professional

Health Products

HOMEOPATHIC

NDC 83027-0068-1

MYCO-SODE

2 FL. OZ (60 ml)